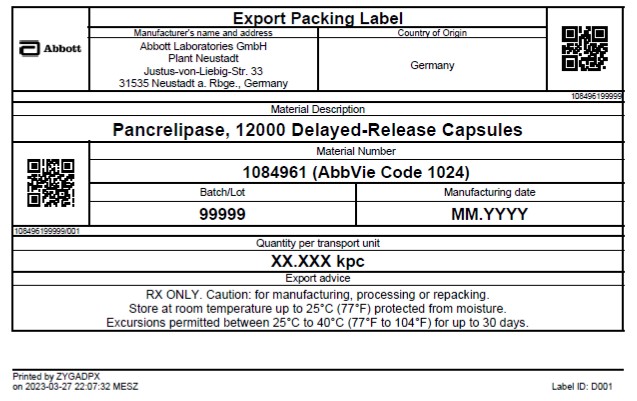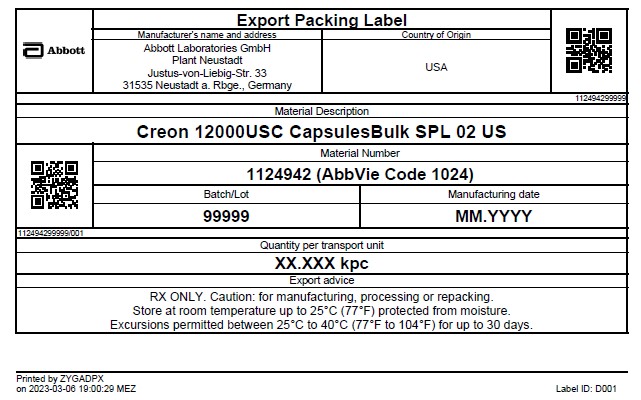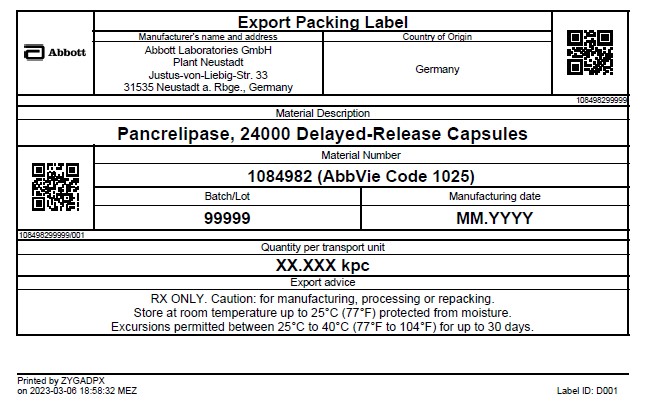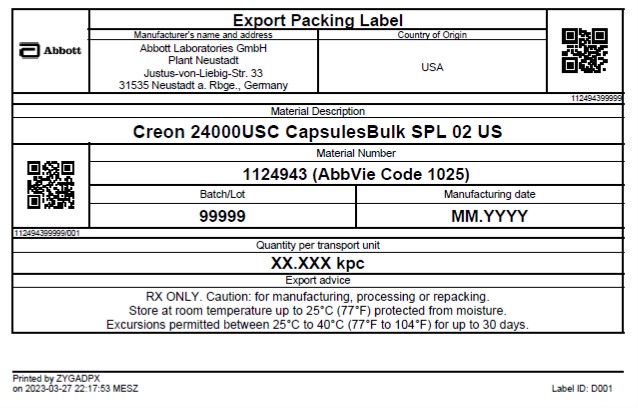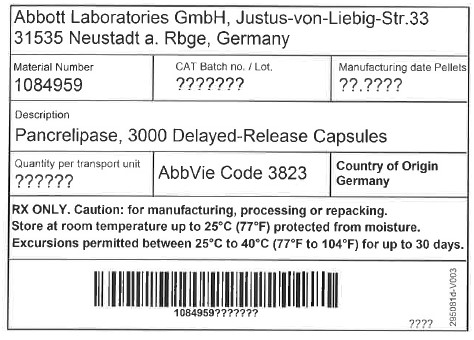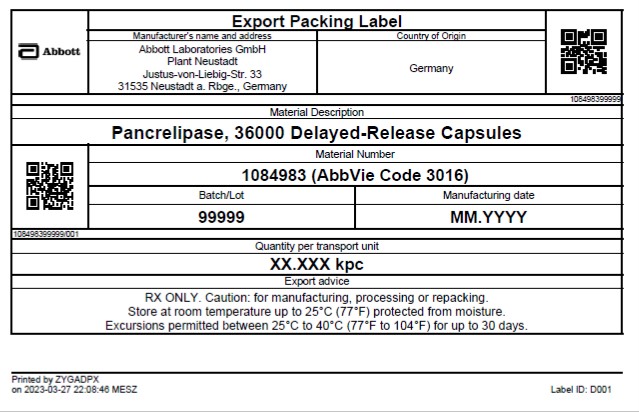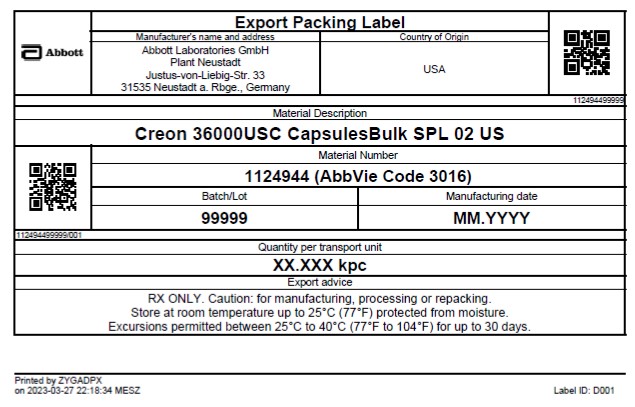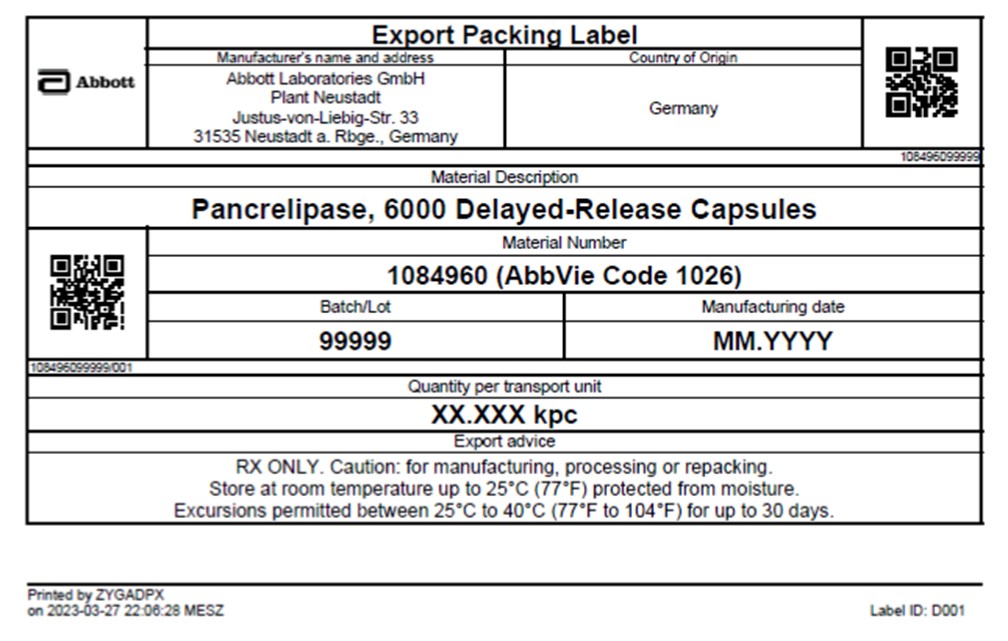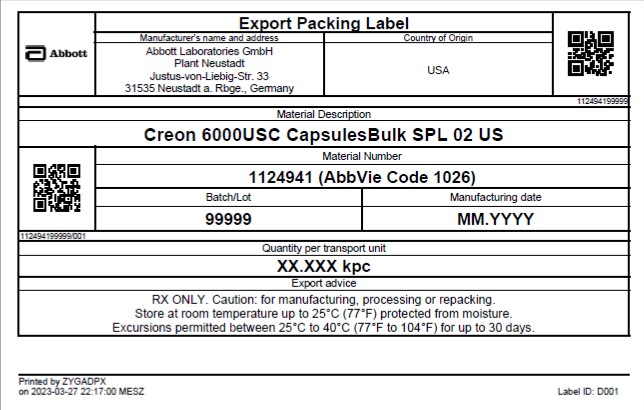 DRUG LABEL: Creon 24000
NDC: 54809-1025 | Form: CAPSULE, DELAYED RELEASE PELLETS
Manufacturer: Abbott Laboratories GmbH
Category: other | Type: BULK INGREDIENT
Date: 20251212

ACTIVE INGREDIENTS: PANCRELIPASE LIPASE 24000 [USP'U]/1 1; PANCRELIPASE PROTEASE 76000 [USP'U]/1 1; PANCRELIPASE AMYLASE 120000 [USP'U]/1 1

Creon Bulk Caspules

Description

Pancrelipase, 3000 Delayed-release Capsules (BULK)

Pancrelipase, 6000 Delayed-release Capsules (BULK)

Pancrelipase, 12000 Delayed-release Capsules (BULK)

Pancrelipase, 24000 Delayed-release Capsules (BULK)

Pancrelipase, 36000 Delayed-release Capsules (BULK)

Caution:

RX ONLY. Caution: for manufacturing, processing or repacking.

Storage and Handling

Store at room temperature up to 25 degrees C (77degrees F) protected from moisture.

Excursions permitted between 25 degrees C to 40 Degrees C (77 degrees F to 104 degrees F) for up to 30 days.